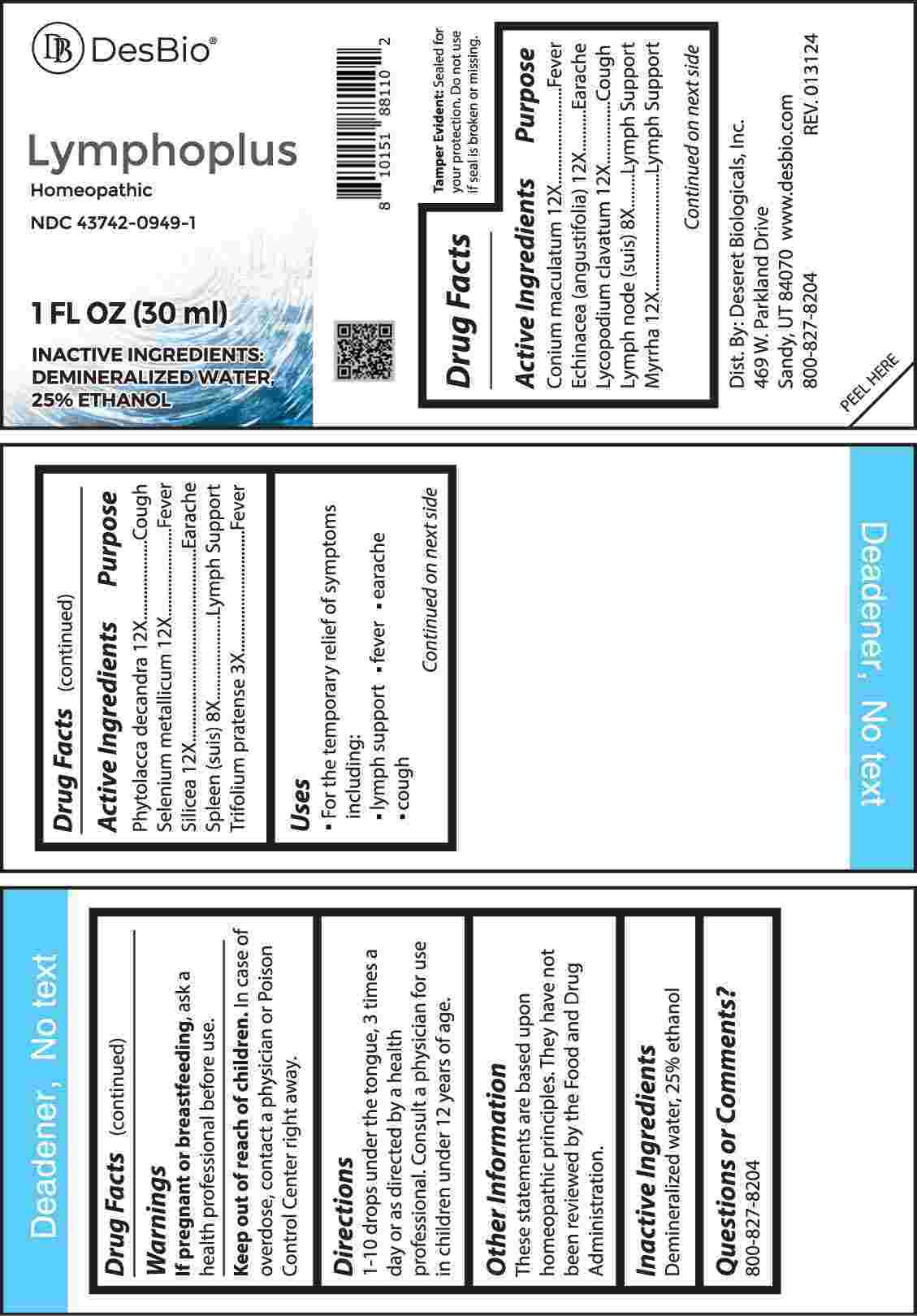 DRUG LABEL: Lymphoplus
NDC: 43742-0949 | Form: LIQUID
Manufacturer: Deseret Biologicals, Inc.
Category: homeopathic | Type: HUMAN OTC DRUG LABEL
Date: 20240508

ACTIVE INGREDIENTS: TRIFOLIUM PRATENSE FLOWER 3 [hp_X]/1 mL; SUS SCROFA LYMPH 8 [hp_X]/1 mL; SUS SCROFA SPLEEN 8 [hp_X]/1 mL; CONIUM MACULATUM FLOWERING TOP 12 [hp_X]/1 mL; ECHINACEA ANGUSTIFOLIA WHOLE 12 [hp_X]/1 mL; LYCOPODIUM CLAVATUM SPORE 12 [hp_X]/1 mL; MYRRH 12 [hp_X]/1 mL; PHYTOLACCA AMERICANA ROOT 12 [hp_X]/1 mL; SELENIUM 12 [hp_X]/1 mL; SILICON DIOXIDE 12 [hp_X]/1 mL
INACTIVE INGREDIENTS: WATER; ALCOHOL

DRUG FACTS:

ACTIVE INGREDIENTS:

Conium Maculatum 12X, Echinacea (Angustifolia) 12X, Lycopodium Clavatum 12X, Lymph Node (Suis) 8X, Myrrha 12X, Phytolacca Decandra 12X, Selenium Metallicum 12X, Silicea 12X, Spleen (Suis) 8X, Trifolium Pratense 3X.

PURPOSE:

Conium Maculatum - Fever, Echinacea (Angustifolia) - Earache, Lycopodium Clavatum - Cough, Lymph Node (Suis) – Lymph Support, Myrrha – Lymph Support, Phytolacca Decandra - Cough, Selenium Metallicum - Fever, Silicea - Earache, Spleen (Suis) – Lymph Support, Trifolium Pratense - Fever

USES:

• For the temporary relief of symptoms including:

• lymph support • fever • earache • cough

These statements are based upon homeopathic principles. They have not been reviewed by the Food and Drug Administration.

WARNINGS:

If pregnant or breast-feeding, ask a health professional before use.

Keep out of reach of children. In case of overdose, contact a physician or Poison Control Center right away.

Tamper Evident: Sealed for your protection. Do not use if seal is broken or missing.

KEEP OUT OF REACH OF CHILDREN:

In case of overdose, contact a physician or Poison Control Center right away.

DIRECTIONS:

1-10 drops under the tongue, 3 times a day or as directed by a health professional. Consult a physician for use in children under 12 years of age.

INACTIVE INGREDIENTS:

Demineralized water, 25% ethanol

QUESTIONS:

Dist. By: Deseret Biologicals, Inc.

469 W. Parkland Drive

Sandy, UT 84070

www.desbio.com

800-827-8204

PACKAGE LABEL DISPLAY:

Des Bio

Lymphoplus

Homeopathic
NDC 43742-0949-1
1 FL OZ (30 ml)